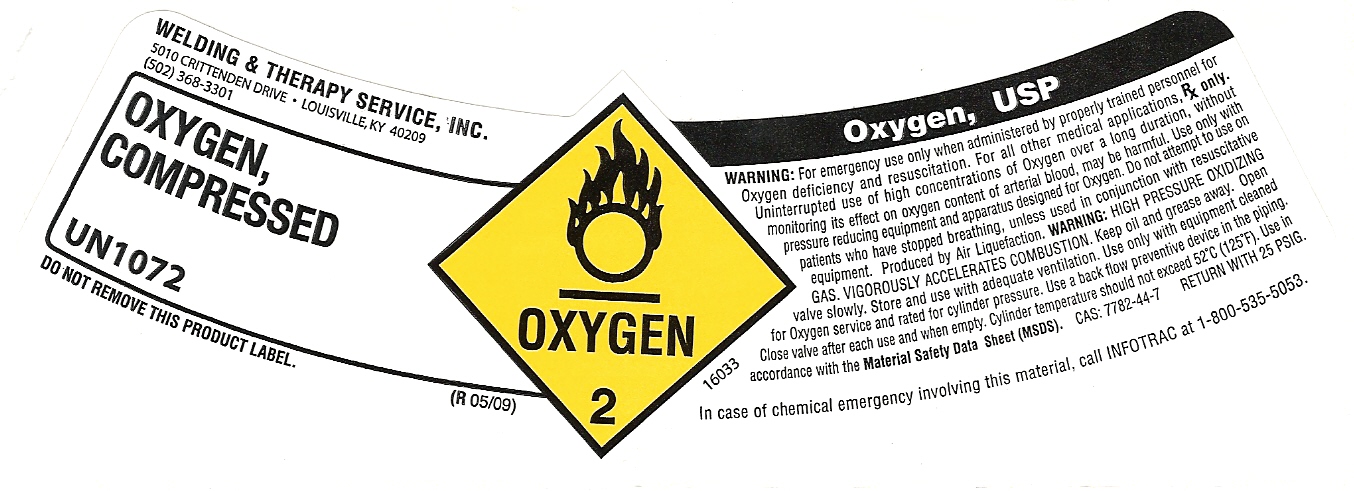 DRUG LABEL: Oxygen
								
NDC: 33344-005 | Form: GAS
Manufacturer: Welding & Therapy Service Inc.
Category: prescription | Type: HUMAN PRESCRIPTION DRUG LABEL
Date: 20110722

ACTIVE INGREDIENTS: Oxygen 99 L/100 L

OXYGEN COMPRESSED LABEL

PACKAGE LABEL

OXYGEN, COMPRESSED
UN1072
DO NOT REMOVE THIS PRODUCT LABEL
OXYGEN 2
OXYGEN, USP
WARNING: For emergency use only when administered by properly trained personnel for
Oxygen deficiency and resuscitation. For all other medical applications, Rx only.
Uninterrupted use of high concentrations of Oxygen over a long duration, without
monitoring its effect on oxygen content of arterial blood, may be harmful. Use only with
pressure reducing equipment and apparatus designed for Oxygen. Do not attempt to use on
patients who have stopped breathing, unless used in conjunction with resuscitative
equipment. Produced by Air Liquefaction. WARNING: HIGH PRESSURE OXIDIZING
GAS. VIGOROUSLY ACCELERATES COMBUSTION. Keep oil and grease away. Open
valve slowly. Store and use with adequate ventilation. Use only with equipment cleaned
for Oxygen service and rated for cylinder pressure. Use a back flow preventive device in piping.
Close valve after each use and when empty. Cylinder temperature should not exceed 52oC (125oF). Use in
accordance with the Material Safety Data Sheet (MSDS). CAS: 77820-44-7 RETURN WITH 25 PSIG.
In case of chemical emergency involving this material, call INFOTRAC at 1-800-535-5053.